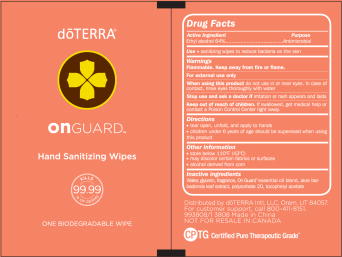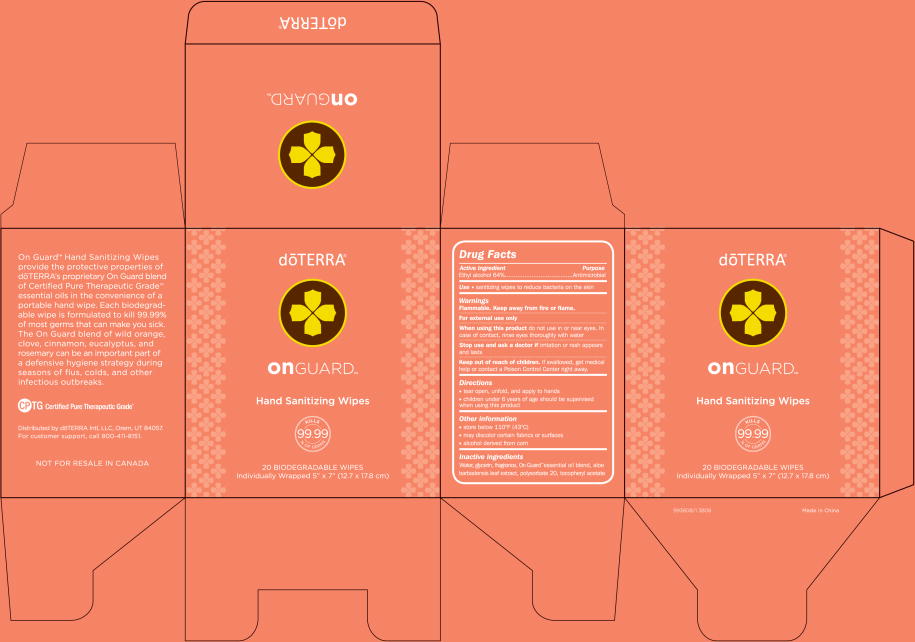 DRUG LABEL: On Guard Hand Sanitizing Wipe
NDC: 49924-1231 | Form: CLOTH
Manufacturer: do Terra
Category: otc | Type: HUMAN OTC DRUG LABEL
Date: 20091101

ACTIVE INGREDIENTS: ALCOHOL 1 ug/1 mL
INACTIVE INGREDIENTS: POLYSORBATE 20 0.8 mg/1 mL; GLYCERIN 96 mg/1 mL; WATER 870.4 mg/1 mL

dōTERRA®
onGUARD™
Hand Sanitizing Wipes

Drug Facts

Active Ingredient

Ethyl alcohol 64%

Purpose

Antimicrobial

Use

- sanitizing wipes to reduce bacteria on the skin.

Warnings

Flammable. Keep away from fire or flame.

For external use only

When using this product do not use in or near eyes. In case of contact, rinse eyes thoroughly with water

Stop use and ask a doctor if irritation or rash appears and lasts

Keep out of reach of children. If swallowed, get medical help or contact a Poison Control Center right away.

Directions

- tear open, unfold, and apply to hands
- children under 6 years of age should be supervised when using this product

Other information

- store below 110°F (43°C)
- may discolor certain fabrics or surfaces
- alcohol derived from corn

Inactive ingredients

Water, glycerin, fragrance, On Guard™ essential oil blend, aloe barbadensis leaf extract, polysorbate 20, tocopheryl acetate

Distributed by dōTERRA Intl, LLC, Orem, UT 84057.
For customer support, call 800-411-8151.
993808/103808 Made in Chine
NOT FOR RESALE IN CANADA
CPTG Certified Pure Therapeutic Grade™

Principal Display Panel – Packet - ONE BIODEGRADABLE WIPE

On Guard Hand Sanitizing Wipes – Packet
dōTERRA®
onGUARD™
Hand Sanitizing Wipes
KILLS 99.99% OF GERMS
ONE BIODEGRADABLE WIPE

Principal Display Panel – Carton - 20 BIODEGRADABLE WIPES

On Guard Hand Sanitizing Wipes – Carton
doōTERRA®
onGUARD™
Hand Sanitizing Wipes
KILLS 99.99% OF GERMS
20 BIODEGRADABLE WIPES
Individually Wrapped 5” x 7” (12.7 x 17.8 cm)